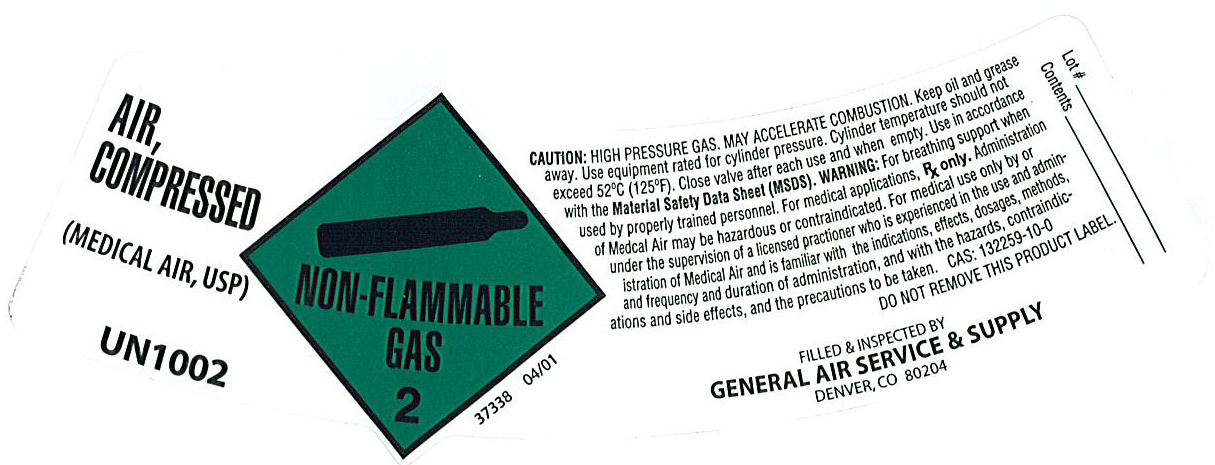 DRUG LABEL: Air
NDC: 21220-124 | Form: GAS
Manufacturer: General Air Service & Supply Co
Category: otc | Type: HUMAN OTC DRUG LABEL
Date: 20100331

ACTIVE INGREDIENTS: Air 990 mL/1 L

air

PACKAGE LABEL

AIR, COMPRESSED (MEDICAL AIR, USP) UN1002
NON-FLAMMABLE GAS 2
37338 04/01
CAUTION: HIGH PRESSURE GAS. MAY ACCELERATE COMBUSTION. Keep oil and grease away. Use equipment rated for cylinder pressure. Cylinder temperature should not exceed 52C (125F). Close valve after each use and when empty. Use in accordance with the Material Safety Data Sheet (MSDS). WARNING: For breathing support when used by properly trained personnel. For medical applications, Rx Only. Administration of Medical Air may be hazardous or contraindicated. For medical use only by under the supervision of a licensed practitioner who is experienced in the use and administration of Medical Air and is familiar with the indications, effects, dosages, methods, and frequency and duration of administration, and with the hazards, contraindication and side effects, and the precautions to be taken. CAS: 132259-10-0 DO NOT REMOVE THIS PRODUCT LABEL.
FILLED and INSPECTED BY GENERAL AIR SERVICE and SUPPLY DENVER CO 80204
LOT #
CONTENTS